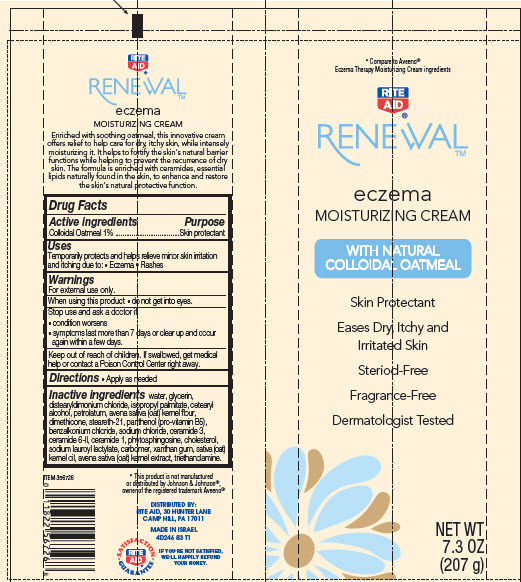 DRUG LABEL: Renewal Eczema Moisturizing
NDC: 11822-2461 | Form: CREAM
Manufacturer: Rite Aid Corporation
Category: otc | Type: HUMAN OTC DRUG LABEL
Date: 20140916

ACTIVE INGREDIENTS: OATMEAL 1 g/100 g
INACTIVE INGREDIENTS: WATER; GLYCERIN; DISTEARYLDIMONIUM CHLORIDE; ISOPROPYL PALMITATE; CETOSTEARYL ALCOHOL; PETROLATUM; DIMETHICONE; STEARETH-21; PANTHENOL; BENZALKONIUM CHLORIDE; CERAMIDE 3; CERAMIDE 6 II; CERAMIDE 1; PHYTOSPHINGOSINE; CHOLESTEROL; SODIUM LAUROYL LACTYLATE; XANTHAN GUM; OAT KERNEL OIL; OAT; SODIUM CHLORIDE; TROLAMINE

Renewal™ Eczema Moisturizing

Active ingredient

Colloidal Oatmeal 1%

Purpose

Skin protectant

Uses

Temporarily protects and helps relieve minor skin irritation and itching due to:

- Eczema
- Rashes

Warnings

For external use only.

When using this product

- do not get into eyes.

Stop use and ask a doctor if

- condition worsens
- symptoms last more than 7 days or clear up and occur again within a few days.

Keep Out of Reach of Children.

If swallowed, get medical help or contact a Poison Control Center right away.

Directions

- Apply as needed

Inactive ingredients

water, glycerin, distearyldimonium chloride, isopropyl palmitate, cetearyl alcohol, petrolatum, avena sativa (oat) kernel flour, dimethicone, steareth-21, panthenol (pro-vitamin B5), benzalkonium chloride, sodium chloride, ceramide 3, ceramide 6-II, ceramide 1, phytosphingosine, cholesterol, sodium lauroyl lactylate, carbomer, xanthan gum, sativa (oat) kernel oil, avena sativa (oat) kernel extract, triethanolamine.

Package/Label Principal Display Panel

*Compare to Aveeno®
Eczema Therapy Moisturizing Cream ingredients

RITE
AID®

RENEWAL™

eczema
MOISTURIZING CREAM

WITH NATURAL
COLLOIDAL OATMEAL

Skin Protectant

Eases Dry, Itchy and
Irritated Skin

Steriod-Free

Fragrance-Free

Dermatologist Tested

NET WT
7.3 OZ
(207 g)

RITE
AID®

RENEWAL™

eczema
MOISTURIZING CREAM

Enriched with soothing oatmeal, this innovative cream offers relief to help care for dry, itchy skin, while intensely moisturizing it. It helps to fortify the skin’s natural barrier functions while helping to prevent the recurrence of dry skin. The formula is enriched with ceramides, essential lipids naturally found in the skin, to enhance and restore the skin’s natural protective function.

*This product is not manufactured or distributed by Johnson & Johnson®, owner of the registered trademark Aveeno®

DISTRIBUTED BY:
RITE AID, 30 HUNTER LANE
CAMP HILL, PA 17011

MADE IN ISRAEL
4D246 83 T1

SATISFACTION
GUARANTEE

IF YOU’RE NOT SATISFIED, WE’LL HAPPILY REFUND YOUR MONEY.

Carton Label